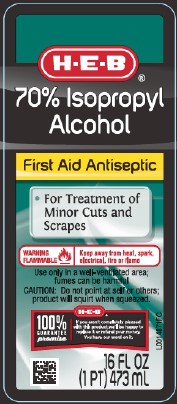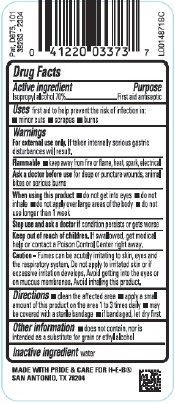 DRUG LABEL: 70%
NDC: 37808-810 | Form: LIQUID
Manufacturer: H E B
Category: otc | Type: HUMAN OTC DRUG LABEL
Date: 20260224

ACTIVE INGREDIENTS: ISOPROPYL ALCOHOL 70 mL/100 mL
INACTIVE INGREDIENTS: WATER

HEB 810.003/810AA
70% Isopropyl Alcohol

Active ingredient

Isopropyl alcohol 70%

Purpose

First Aid Antiseptic

Use

first aid to help prevent the risk of infection in:

- minor cuts
- scrapes
- burns

Warnings

For external use only.If taken internally serious gastric disturbances will result.

Flammable

- Keep away from fire or flame, heat, spark, electrical

Ask a Doctor before use

for deep or puncture wounds, animal bites or serious burns

When using this product

- do not get into eyes
- do not inhale
- do not apply over large areas of the body
- do not use longer than 1 week

Stop use and ask a doctor if

condition persists or gets worse

Keep out of reach of children

If swallowed, get medical help or contact a Poison Control Center right away.

Caution

Fumes can be acutely irritating to skin, eyes and the respiratory system. Do not apply to irritated skin or if excessive irritation develops. Avoid getting into the eyes or on mucous membranes. Avoid inhaling this product.

Directions

- clean the affected area
- apply a small amount of this product on the affected area 1 to 3 times daily
- may be covered with a sterile bandage
- if bandaged, let dry first

Other information

- does not contain, nor is intended as a substitute for grain or ethyl alcohol

Inactive ingredient

water

ADVERSE REACTION

MADE WITH PRIDE & CARE FOR H-E-B

SAN ANTONIO, TX 78204

Pat. D675, 101

principal display panel

H-E-B®

70% Isopropyl Alcohol

First Aid Antiseptic

- Decreases Germs in Minor Cuts and Scrapes

WARNING FLAMMABLE - Keep away from heat, spark, electrical, fire or flame

Use only in a well-ventilated Area; fumes can be harmful

CAUTION: Do not point at self or others; product will squirt when squeezed.

H-E-B®100% GUARANTEE promise

If you aren't completely pleased with this product, we'll be happy to replace it or refund your money. You have our word on it.

16 FL OZ (1 PT) 473 mL